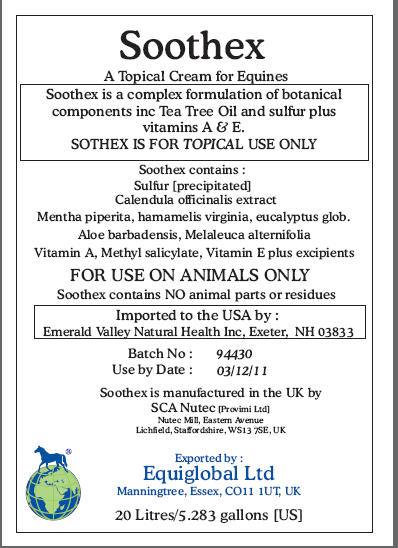 DRUG LABEL: Soothex
NDC: 52338-667 | Form: CREAM
Manufacturer: SCA NuTec
Category: animal | Type: PRESCRIPTION ANIMAL DRUG LABEL
Date: 20100419

ACTIVE INGREDIENTS: SULFUR 100 mg/1 mL; TEA TREE OIL 10 mg/1 mL; EUCALYPTUS GLOBULUS LEAF 20 mg/1 mL; WITCH HAZEL 20 mg/1 mL; ALOE VERA LEAF 15 mg/1 mL; CALENDULA OFFICINALIS FLOWER 25 mg/1 mL; VITAMIN A 1000 [iU]/1 mL; METHYL SALICYLATE 2 mg/1 mL; VITAMIN E 2.6 mg/1 mL

Soothex

A Topical Cream for Equines

Soothex is a complex formulation of botanical
components inc Tea Tree Oil and sulfur plus
vitamins A and E.
SOTHEX IS FOR TOPICAL USE ONLY

Soothex contains:
Sulfur [precipitated]
Calendula officinalis extract
Mentha piperita, hamamelis virginia, eucalyptus glob.
Aloe barbadensis, Melaleuca alternifolia
Vitamin A, Methyl salicylate, Vitamin E plus excipients

WARNINGS

FOR USE ON ANIMALS ONLY

Soothex contains NO animal parts or residues

Imported to the USA by :
Emerald Valley Natural Health Inc, Exeter, NH 03833
Batch No: 94430
Use by Date : 03/12/11
Soothex is manufactured in the UK by
SCA Nutec [Provimi Ltd]
Nutec Mill, Eastern Avenue
Lichfield, Staffordshire, WS13 7SE, UK
Exported by :
Equiglobal Ltd
Manningtree, Essex, CO11 1UT, UK
20 Litres/5.283 gallons [US]